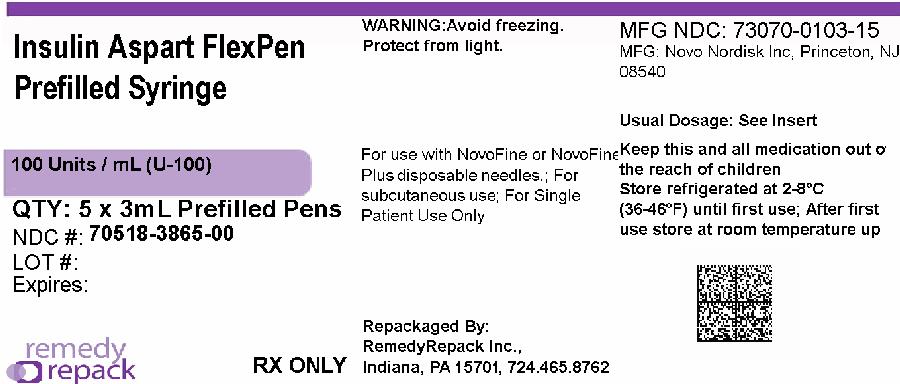 DRUG LABEL: Insulin Aspart
NDC: 70518-3865 | Form: INJECTION, SOLUTION
Manufacturer: REMEDYREPACK INC.
Category: prescription | Type: HUMAN PRESCRIPTION DRUG LABEL
Date: 20260114

ACTIVE INGREDIENTS: INSULIN ASPART 100 [iU]/1 mL
INACTIVE INGREDIENTS: SODIUM PHOSPHATE, DIBASIC, DIHYDRATE 1.25 mg/1 mL; GLYCERIN 16 mg/1 mL; HYDROCHLORIC ACID; METACRESOL 1.72 mg/1 mL; PHENOL 1.5 mg/1 mL; SODIUM CHLORIDE 0.58 mg/1 mL; SODIUM HYDROXIDE; ZINC 19.6 ug/1 mL

HIGHLIGHTS OF PRESCRIBING INFORMATION

These highlights do not include all the information needed to use INSULIN ASPART safely and effectively.
See full prescribing information for INSULIN ASPART.
INSULIN ASPART injection, for subcutaneous or intravenous use
Initial U.S. Approval: 2000
This product is NovoLog (insulin aspart).

1 INDICATIONS AND USAGE

Insulin Aspart is rapid acting human insulin analog indicated to improve glycemic control in adults and pediatric patients with diabetes mellitus (1).

2 DOSAGE AND ADMINISTRATION

See Full Prescribing Information for important preparation, administration, and dosage instructions (2.1, 2.2, 2.3, 2.4, 2.5).

- Subcutaneous injection (2.2):
- Inject subcutaneously within 5-10 minutes before a meal into the abdominal area, thigh, buttocks or upper arm.
- Rotate injection sites within the same region from one injection to the next to reduce risk of lipodystrophy and localized cutaneous amyloidosis.
- Should generally be used in regimens with an intermediate- or long-acting insulin.
- Continuous Subcutaneous Infusion (Insulin Pump) (2.2):
- Refer to the insulin infusion pump user manual to see if NovoLog (insulin aspart) can be used. Use in accordance with the insulin pump instructions for use.
- Administer by continuous subcutaneous infusion using an insulin pump in a region recommended in the instructions from the pump manufacturer.
- Rotate the injection sites within the same region from one injection to the next to reduce the risk of lipodystrophy and localized cutaneous amyloidosis.
- Do not mix with other insulins or diluents in the pump.
- Intravenous Administration (2.2) :
- Dilute Insulin Aspart to concentrations from 0.05 unit/mL to 1 unit/mL insulin aspart in infusion systems using polypropylene infusion bags.
- Insulin Aspart is stable in infusion fluids such as 0.9% Sodium Chloride Injection, USP.
- Individualize and adjust the dosage of Insulin Aspart based on route of administration, the individual's metabolic needs, blood glucose monitoring results and glycemic control goal (2.4).
- Dosage adjustments may be needed with changes in physical activity, changes in meal patterns (i.e., macronutrient content or timing of food intake), changes in renal or hepatic function or during acute illness (2.4).

3 DOSAGE FORMS AND STRENGTHS

Injection: 100 units/mL (U-100) of insulin aspart available as:

- 3 mL single-patient-use PenFill®prefilled cartridge for the 3 mL PenFill cartridge device (3)
- 3 mL single-patient-use FlexPen®prefilled pen (3)

4 CONTRAINDICATIONS

- During episodes of hypoglycemia (4).
- Hypersensitivity to Insulin Aspart or one of its excipients.

5 WARNINGS AND PRECAUTIONS

- Never sharea Insulin Aspart FlexPen, PenFill cartridge or PenFill cartridge device between patients, even if the needle is changed (5.1).
- Hyperglycemia or hypoglycemia with changes in insulin regimen:Make changes to a patient’s insulin regimen (e.g., insulin strength, manufacturer, type, injection site or method of administration) under close medical supervision with increased frequency of blood glucose monitoring (5.2).
- Hypoglycemia:May be life-threatening. Increase frequency of glucose monitoring with changes to: insulin dosage, concomitantly administered glucose lowering medications, meal pattern, physical activity; and in patients with renal or hepatic impairments and hypoglycemia unawareness (5.3).
- Medication Errors:Accidental mix-ups between insulin products can occur. Instruct patients to check insulin labels before injection (5.4).
- Hypersensitivity reactions:Severe, life-threatening, generalized allergy, including anaphylaxis, may occur. Discontinue Insulin Aspart, treat, and monitor, if indicated (5.5).
- Hypokalemia:May be life-threatening. Monitor potassium levels in patients at risk of hypokalemia and treat if indicated (5.6).
- Fluid retention and heart failure with concomitant use of thiazolidinediones (TZDs):Observe for signs and symptoms of heart failure; consider dosage reduction or discontinuation if heart failure occurs (5.7).
- Hyperglycemia and Ketoacidosis Due to Insulin Pump Device Malfunction:Monitor glucose and administer Insulin Aspart by subcutaneous injection if pump malfunction occurs (5.8).

6 ADVERSE REACTIONS

Adverse reactions observed with Insulin Aspart include: hypoglycemia, allergic reactions, local injection site reactions, lipodystrophy, rash, and pruritus (6).

To report SUSPECTED ADVERSE REACTIONS, contact Novo Nordisk Pharma, Inc. at 1-800-727-6500 or FDA at 1-800-FDA-1088 or www.fda.gov/medwatch.

7 DRUG INTERACTIONS

- Drugs that may increase the risk of hypoglycemia:antidiabetic agents, ACE inhibitors, angiotensin II receptor blocking agents, disopyramide, fibrates, fluoxetine, monoamine oxidase inhibitors, pentoxifylline, pramlintide, salicylates, somatostatin analog (e.g., octreotide), and +sulfonamide antibiotics (7).
- Drugs that may decrease the blood glucose lowering effect:atypical antipsychotics, corticosteroids, danazol, diuretics, estrogens, glucagon, isoniazid, niacin, oral contraceptives, phenothiazines, progestogens (e.g., in oral contraceptives), protease inhibitors, somatropin, sympathomimetic agents (e.g., albuterol, epinephrine, terbutaline), and thyroid hormones (7).
- Drugs that may increase or decrease the blood glucose lowering effect:alcohol, beta-blockers, clonidine, lithium salts, and pentamidine (7).
- Drugs that may blunt the signs and symptoms of hypoglycemia:beta-blockers, clonidine, guanethidine, and reserpine (7).

8 USE IN SPECIFIC POPULATIONS

Pediatric: Has not been studied in children with type 2 diabetes. Has not been studied in children with type 1 diabetes <2 years of age (8.4).

FULL PRESCRIBING INFORMATION

1 INDICATIONS AND USAGE

Insulin Aspart is indicated to improve glycemic control in adults and pediatric patients with diabetes mellitus.

2 DOSAGE AND ADMINISTRATION

2.1 Important Preparation and Administration Instructions

- Always check insulin labels before administration. This product is NovoLog (insulin aspart) [see Warnings and Precautions (5.4)] .
- Inspect Insulin Aspart visually before use. It should appear clear and colorless. Do not use Insulin Aspart if particulate matter or coloration is seen.
- In patients with visual impairment, use:
  - Insulin Aspart FlexPen with caution in those who may rely on audible clicks to dial
- their dose.
  1. PenFill cartridges with caution.
- Do notmix Insulin Aspart with other insulins when administering using a continuous subcutaneous infusion pump.

2.2 Preparation and Administration Instructions for the Approved Routes of Administration

Subcutaneous Injection

- Inject Insulin Aspart subcutaneously within 5-10 minutes before a meal into the abdominal area, thigh, buttocks or upper arm.
- Rotate injection sites within the same region from one injection to the next to reduce the risk of lipodystrophy and localized cutaneous amyloidosis. Do not inject into areas of lipodystrophy or localized cutaneous amyloidosis [see Warnings and Precautions (5.2) and Adverse Reactions (6.1, 6.3)].
- Dial the Insulin Aspart FlexPen dials in 1-unit increments.
- Generally use Insulin Aspart (administered by subcutaneous injection) in regimens with an intermediate- or long-acting insulin.
- May dilute this Insulin Aspart product with Insulin Diluting Medium for NovoLog for subcutaneous injection. Diluting one part Insulin Aspart to:
  - Nine parts diluent will yield a concentration one-tenth that of Insulin Aspart (equivalent to U-10).
  - One part diluent will yield a concentration one-half that of Insulin Aspart (equivalent to U-50).

Continuous Subcutaneous Infusion (Insulin Pump)

- Can use this Insulin Aspart product with the continuous subcutaneous insulin infusion pumps labeled for use with NovoLog (insulin aspart). Refer to the insulin pump user manual to see if NovoLog can be used. Use Insulin Aspart in accordance with the insulin pump system’s instructions for use.
- Train patients using continuous subcutaneous insulin infusion pump therapy to administer insulin by injection and have alternate insulin therapy available in case of pump failure.
- Administer Insulin Aspart by continuous subcutaneous infusion in a region recommended in the instructions from the pump manufacturer. Rotate infusion sites within the same region to reduce the risk of lipodystrophy or localized cutaneous amyloidosis [see Warnings and Precautions (5.2) and Adverse Reactions (6.1, 6.3)].
- Instruct patients to follow healthcare provider recommendations when setting basal and meal time infusion rate.
- Change the Insulin Aspart in the reservoir at least every 7 days or according to the pump user manual, whichever is shorter. Follow the NovoLog-specific information for in-use time because NovoLog-specific information may differ from general pump manual instructions.
- Change the infusion set and the infusion set insertion site according to the manufacturer’s user manual.
- Do notdilute or mix Insulin Aspart when administering by continuous subcutaneous infusion.
- Do notexpose Insulin Aspart in the pump reservoir to temperatures greater than 98.6°F (37°C).

Intravenous Administration

- Administer Insulin Aspart intravenously only under medical supervision with close monitoring of blood glucose and potassium levels to avoid hypoglycemia and hypokalemia [see Warnings and Precautions (5.3, 5.6) and How Supplied/Storage and Handling (16.2)].
- Dilute Insulin Aspart to concentrations from 0.05 unit/mL to 1 unit/mL insulin aspart in infusion systems using polypropylene infusion bags. Insulin Aspart is stable in infusion fluids such as 0.9% Sodium Chloride Injection, USP.

2.3 Dosage Recommendations

- Individualize the dosage of Insulin Aspart based on the route of administration, the patient’s metabolic needs, blood glucose monitoring results and glycemic control goal.
- Dosage adjustments may be needed with changes in physical activity, changes in meal patterns (i.e., macronutrient content or timing of food intake), changes in renal or hepatic function or during acute illness [see Warnings and Precautions (5.2, 5.3) and Use in Specific Populations (8.6, 8.7)] .
- When switching from another insulin to Insulin Aspart, a different dosage of Insulin Aspart may be needed [see Warnings and Precautions (5.2)] .
- During changes to a patient’s insulin regimen, increase the frequency of blood glucose monitoring [see Warnings and Precautions (5.2)].

2.4 Dosage Modifications for Drug Interactions

Dosage modification may be needed when Insulin Aspart is used concomitantly with certain drugs [see Drug Interactions (7)].

2.5 Instructions for Mixing Insulin Aspart with Other Insulins

The table below includes instructions regarding mixing Insulin Aspart with other insulins.

Subcutaneous injection route | - Insulin Aspart may onlybe mixed with NPH insulin preparations.; •If Insulin Aspart is mixed with NPH insulin, withdraw Insulin Aspart into the syringe first and inject immediately after mixing.
Continuous subcutaneous infusion route (Insulin Pump) | Do notmix Insulin Aspart with any other insulin.

3 DOSAGE FORMS AND STRENGTHS

Injection: 100 units/mL (U-100) is a clear and colorless solution available as:

- 10 mL multiple-dose vial
- 3 mL single-patient-use PenFill prefilled cartridges for the 3 mL PenFill cartridge delivery device with NovoFine®disposable needles
- 3 mL single-patient-use FlexPen prefilled pen

4 CONTRAINDICATIONS

Insulin Aspart is contraindicated:

- During episodes of hypoglycemia [see Warnings and Precautions (5.3)]
- In patients with hypersensitivity to Insulin Aspart or one of its excipients, [see Warnings and Precautions (5.5)]

5 WARNINGS AND PRECAUTIONS

5.1 Never Share a Insulin Aspart FlexPen, PenFill Cartridge, or PenFill Cartridge Device between Patients

Insulin Aspart FlexPen, PenFill cartridge, and PenFill cartridge devices should never be shared between patients, even if the needle is changed. Patients using Insulin Aspart vials must never share needles or syringes with another person. Sharing poses a risk for transmission of blood-borne pathogens.

5.2 Hyperglycemia or Hypoglycemia with Changes in Insulin Regimen

Changes in an insulin regimen (e.g., insulin strength, manufacturer, type, injection site or method of administration) may affect glycemic control and predispose to hypoglycemia [see Warnings and Precautions (5.3)] or hyperglycemia. Repeated insulin injections into areas of lipodystrophy or localized cutaneous amyloidosis have been reported to result in hyperglycemia; and a sudden change in the injection site (to an unaffected area) has been reported to result in hypoglycemia [see Adverse Reactions (6.1, 6.3)]. Make any changes to a patient’s insulin regimen under close medical supervision with increased frequency of blood glucose monitoring. Advise patients who have repeatedly injected into areas of lipodystrophy or localized cutaneous amyloidosis to change the injection site to unaffected areas and closely monitor for hypoglycemia. For patients with type 2 diabetes, dosage adjustments of concomitant anti-diabetic products may be needed.

5.3 Hypoglycemia

Hypoglycemia is the most common adverse reaction of all insulins, including Insulin Aspart. Severe hypoglycemia can cause seizures, may lead to unconsciousness, may be life threatening or cause death. Hypoglycemia can impair concentration ability and reaction time; this may place an individual and others at risk in situations where these abilities are important (e.g., driving or operating other machinery).

Hypoglycemia can happen suddenly and symptoms may differ in each individual and change over time in the same individual. Symptomatic awareness of hypoglycemia may be less pronounced in patients with longstanding diabetes in patients with diabetic nerve disease, in patients using medications that block the sympathetic nervous system (e.g., beta-blockers) [see Drug Interactions (7)] , or in patients who experience recurrent hypoglycemia.

Risk Factors for Hypoglycemia

The risk of hypoglycemia after an injection is related to the duration of action of the insulin and, in general, is highest when the glucose lowering effect of the insulin is maximal. As with all insulins, the glucose lowering effect time course of Insulin Aspart may vary in different individuals or at different times in the same individual and depends on many conditions, including the area of injection as well as the injection site blood supply and temperature [see Clinical Pharmacology (12.2)] . Other factors which may increase the risk of hypoglycemia include changes in meal pattern (e.g., macronutrient content or timing of meals), changes in level of physical activity, or changes to concomitantly administered medication [see Drug Interactions (7)] . Patients with renal or hepatic impairment may be at higher risk of hypoglycemia [see Use in Specific Populations (8.6, 8.7)].

Risk Mitigation Strategies for Hypoglycemia

Patients and caregivers must be educated to recognize and manage hypoglycemia. Self-monitoring of blood glucose plays an essential role in the prevention and management of hypoglycemia; increased frequency of blood glucose monitoring is recommended. In patients at higher risk for hypoglycemia and patients who have reduced symptomatic awareness of hypoglycemia; increased frequency of blood glucose monitoring is recommended.

5.4 Hypoglycemia Due to Medication Errors

Accidental mix-ups between insulin products have been reported. To avoid medication errors between this Insulin Aspart product and other insulins, instruct patients to always check the insulin label before each injection.

5.5 Hypersensitivity Reactions

Severe, life-threatening, generalized allergy, including anaphylaxis, can occur with insulins, including Insulin Aspart. If hypersensitivity reactions occur, discontinue Insulin Aspart; treat per standard of care and monitor until symptoms and signs resolve [see Adverse Reactions (6)]. Insulin Aspart is contraindicated in patients who have had hypersensitivity reactions to insulin aspart or one of the excipients [see Contraindications (4)].

5.6 Hypokalemia

All insulins, including Insulin Aspart, can cause a shift in potassium from the extracellular to intracellular space, possibly leading to hypokalemia. Untreated hypokalemia may cause respiratory paralysis, ventricular arrhythmia, and death. Monitor potassium levels in patients at risk for hypokalemia if indicated (e.g., patients using potassium-lowering medications, patients taking medications sensitive to serum potassium concentration).

5.7 Fluid Retention and Heart Failure with Concomitant Use of PPAR-gamma Agonists

Thiazolidinediones (TZDs), which are peroxisome proliferator-activated receptor (PPAR)-gamma agonists, can cause dose-related fluid retention, particularly when used in combination with insulin. Fluid retention may lead to or exacerbate heart failure. Patients treated with insulin, including Insulin Aspart, and a PPAR-gamma agonist should be observed for signs and symptoms of heart failure. If heart failure develops, it should be managed according to current standards of care, and discontinuation or dose reduction of the PPAR-gamma agonist must be considered.

5.8 Hyperglycemia and Ketoacidosis Due to Insulin Pump Device Malfunction

Malfunction of the insulin pump or insulin infusion set or insulin degradation can rapidly lead to hyperglycemia and ketoacidosis. Prompt identification and correction of the cause of hyperglycemia or ketosis is necessary. Interim subcutaneous injections with Insulin Aspart may be required. Patients using continuous subcutaneous insulin infusion pump therapy must be trained to administer insulin by injection and have alternate insulin therapy available in case of pump failure [see How Supplied/Storage and Handling (16.2) and Patient Counseling Information (17)] .

6 ADVERSE REACTIONS

1. The following adverse reactions are also discussed elsewhere:
2. Hypoglycemia [see Warnings and Precautions (5.3)]
3. Hypoglycemia Due to Medication Errors [see Warnings and Precautions (5.4)]
4. Hypersensitivity reactions [see Warnings and Precautions (5.5)]
5. Hypokalemia [see Warnings and Precautions (5.6)]

6.1 Clinical Trial Experience

1. Because clinical trials are conducted under widely varying designs, the adverse reaction rates reported in one clinical trial may not be easily compared to those rates reported in another clinical trial, and may not reflect the rates actually observed in clinical practice. The safety of Insulin Aspart was evaluated in two treat-to-target trials of 6 months duration, conducted in patients with type 1 diabetes or type 2 diabetes [see Clinical Studies (14)].
2. The data in Table 1 reflect the exposure of 596 patients with type 1 diabetes to Insulin Aspart in one clinical trial with a mean exposure duration to Insulin Aspart of 24 weeks. The mean age was 39 years. Fifty-one percent were male, 94% were Caucasian, 2% were Black and 4% were other races. The mean body mass index (BMI) was 25.6 kg/m^2. The mean duration of diabetes was 15.7 years and the mean HbA1cat baseline was 7.9%.
3. The data in Table 2 reflect the exposure of 91 patients with type 2 diabetes to Insulin Aspart in one clinical trial with a mean exposure duration to Insulin Aspart of 24 weeks. The mean age was 57 years. Sixty-three percent were male, 76% were Caucasian, 9% were Black and 15% were other races. The mean BMI was 29.7 kg/m^2. The mean duration of diabetes was 12.7 years and the mean HbA1cat baseline was 8.1%.

Common adverse reactions were defined as events that occurred in ≥5%, excluding hypoglycemia, of the population studied. Common adverse events that occurred at the same rate or greater for Insulin Aspart-treated patients than in comparator-treated patients during clinical trials in patients with type 1 diabetes mellitus and type 2 diabetes mellitus (other than hypoglycemia) are listed in Table 1 and Table 2, respectively.

Table 1: Adverse reactions that occurred in≥ 5% of Type 1 Diabetes Mellitus Adult Patients treated with Insulin Aspart and at the same rate or greater on Insulin Aspart than on comparator

 | Insulin Aspart + NPH (%) (n= 596) | Regular Human Insulin + NPH (%) (n= 286)
Headache | 12 | 10
Injury accidental | 11 | 10
Nausea | 7 | 5
Diarrhea | 5 | 3

Table 2: Adverse reactions that occurred in≥ 5% of Type 2 Diabetes Mellitus Adult Patients treated with Insulin Aspart and at the same rate or greater on Insulin Aspart than on comparator

 | Insulin Aspart + NPH (%) (n= 91) | Human Regular Insulin + NPH (%) (n= 91)
Hyporeflexia | 11 | 7
Onychomycosis | 10 | 5
Sensory disturbance | 9 | 7
Urinary tract infection | 8 | 7
Chest pain | 5 | 3
Headache | 5 | 3
Skin disorder | 5 | 2
Abdominal pain | 5 | 1
Sinusitis | 5 | 1

Severe Hypoglycemia

Hypoglycemia is the most commonly observed adverse reaction in patients using insulin, including Insulin Aspart .The rates of reported hypoglycemia depend on the definition of hypoglycemia used, diabetes type, insulin dose, intensity of glucose control, background therapies, and other intrinsic and extrinsic patient factors. For these reasons, comparing rates of hypoglycemia in clinical trials for Insulin Aspart with the incidence of hypoglycemia for other products may be misleading and also, may not be representative of hypoglycemia rates that will occur in clinical practice.

Severe hypoglycemia was defined as hypoglycemia associated with central nervous system symptoms and requiring the intervention of another person or hospitalization. The incidence of severe hypoglycemia in:

- Adult and pediatric patients with type 1 diabetes mellitus who received subcutaneous Insulin Aspart was 17% at 24 weeks and 6% at 24 weeks, respectively [see Clinical Studies (14)] .
- Adult patients with type 2 diabetes mellitus who received subcutaneous Insulin Aspart was 10% at 24 weeks.
- Adult and pediatric patients with type 1 diabetes mellitus, who received Insulin Aspart via continuous subcutaneous insulin infusion by external pump was 2% at 16 weeks and 10% at 16 weeks respectively.

No severe hypoglycemic episodes were reported in adult patients with type 2 diabetes mellitus receiving Insulin Aspart via continuous subcutaneous insulin infusion by external pump at 16 weeks.

Allergic Reactions

Some patients taking insulin, including Insulin Aspart have experienced erythema, local edema, and pruritus at the site of injection. These conditions were usually self-limiting. Severe cases of generalized allergy (anaphylaxis) have been reported.

Adverse Reactions Associated with Insulin Initiation and Glucose Control Intensification

Intensification or rapid improvement in glucose control has been associated with a transitory, reversible ophthalmologic refraction disorder, worsening of diabetic retinopathy, and acute painful peripheral neuropathy. However, long-term glycemic control decreases the risk of diabetic retinopathy and neuropathy.

Lipodystrophy

Administration of insulin, including Insulin Aspart, subcutaneously and via subcutaneous insulin infusion by external pump, has resulted in lipoatrophy (depression in the skin) or lipohypertrophy (enlargement or thickening of tissue) in some patients [see Dosage and Administration (2.2)].

Peripheral Edema

Insulins, including Insulin Aspart, may cause sodium retention and edema, particularly if previously poor metabolic control is improved by intensified insulin therapy.

Weight Gain

Weight gain has occurred with insulins including Insulin Aspart and has been attributed to the anabolic effects of insulin and the decrease in glucosuria.

6.2 Immunogenicity

As with all therapeutic proteins, there is potential for immunogenicity. The detection of antibody formation is highly dependent on the sensitivity and specificity of the assay. Additionally, the observed incidence of antibody (including neutralizing antibody) positivity in an assay may be influenced by several factors including assay methodology, sample handling, timing of sample collection, concomitant medications, and underlying disease. For these reasons, comparison of the incidence of antibodies to Insulin Aspart in the studies described below with the incidence of antibodies in other studies or to other products may be misleading.

In a 6-month study with a 6-month extension in adult subjects with type 1 diabetes, 99.8% of patients who received Insulin Aspart were positive for anti-insulin antibodies (AIA) at least once during the study, including 97.2% that were positive at baseline. A total of 92.1% of patients who received Insulin Aspart were positive for anti-drug antibodies (ADA) at least once during the study, including 64.6% that were positive at baseline.

In a phase 3 type 1 diabetes clinical trial of Insulin Aspart, initial increase in titers of antibodies to insulin, followed by a decrease to baseline values, was observed in regular human insulin and insulin aspart treatment groups with similar incidences. These antibodies did not cause deterioration in glycemic control or necessitate increases in insulin dose.

6.3 Post Marketing Experience

The following adverse reactions have been identified during post-approval use of Insulin Aspart. Because these adverse reactions are reported voluntarily from a population of uncertain size, it is generally not possible to reliably estimate their frequency or establish a causal relationship to drug exposure.

Medication errors have been reported in which other insulins have been accidentally substituted for Insulin Aspart.

Localized cutaneous amyloidosis at the injection site has occurred with insulin aspart. Hyperglycemia has been reported with repeated insulin injections into areas of localized cutaneous amyloidosis; hypoglycemia has been reported with a sudden change to an unaffected injection site.

7 DRUG INTERACTIONS

The table below presents clinically significant drug interactions with Insulin Aspart.

Drugs That May Increase the Risk of Hypoglycemia
Drugs: | Antidiabetic agents, ACE inhibitors, angiotensin II receptor blocking agents, disopyramide, fibrates, fluoxetine, monoamine oxidase inhibitors, pentoxifylline, pramlintide, salicylates, somatostatin analog (e.g., octreotide), and sulfonamide antibiotics.
Intervention: | Dose adjustment and increased frequency of glucose monitoring may be required when Insulin Aspart is concomitantly administered with these drugs.
Drugs That May Decrease the Blood Glucose Lowering Effect of Insulin Aspart
Drugs: | Atypical antipsychotics (e.g., olanzapine and clozapine), corticosteroids, danazol, diuretics, estrogens, glucagon, isoniazid, niacin, oral contraceptives, phenothiazines, progestogens (e.g., in oral contraceptives), protease inhibitors, somatropin, sympathomimetic agents (e.g., albuterol, epinephrine, terbutaline), and thyroid hormones.
Intervention: | Dose adjustment and increased frequency of glucose monitoring may be required when Insulin Aspart is concomitantly administered with these drugs.
Drugs That May Increase or Decrease the Blood Glucose Lowering Effect of Insulin Aspart
Drugs: | Alcohol, beta-blockers, clonidine, and lithium salts. Pentamidine may cause hypoglycemia, which may sometimes be followed by hyperglycemia. Pentamidine may cause hypoglycemia, which may sometimes be followed by hyperglycemia.
Intervention: | Dose adjustment and increased frequency of glucose monitoring may be required when Insulin Aspart is concomitantly administered with these drugs.
Drugs That May Blunt Signs and Symptoms of Hypoglycemia
Drugs: | Beta-blockers, clonidine, guanethidine and reserpine
Intervention: | Increased frequency of glucose monitoring may be required when Insulin Aspart is concomitantly administered with these drugs.

8 USE IN SPECIFIC POPULATIONS

8.1 Pregnancy

Risk Summary

Available information from published randomized controlled trials with insulin aspart use during the second trimester of pregnancy have not reported an association with insulin aspart and major birth defects or adverse maternal or fetal outcomes [see Data]. There are risks to the mother and fetus associated with poorly controlled diabetes in pregnancy [see Clinical Considerations].

In animal reproduction studies, administration of subcutaneous insulin aspart to pregnant rats and rabbits during the period of organogenesis did not cause adverse developmental effects at exposures 8-times and equal to the human subcutaneous dose of 1 unit/kg/day, respectively.

Pre- and post-implantation losses and visceral/skeletal abnormalities were seen at higher exposures, which are considered secondary to maternal hypoglycemia. These effects were similar to those observed in rats administered regular human insulin [see Data].

In the U.S. general population, the estimated background risk of major birth defects

and miscarriage in clinically recognized pregnancies is 2 to 4% and 15 to 20%, respectively.

The estimated background risk of major birth defects is 6 to 10% in women with pre-gestational

diabetes with a periconceptional HbA1c>7% and has been reported to be as high as 20 to 25% in women with a periconceptional HbA1c>10%. The estimated background risk of miscarriage for the indicated population is unknown.

Clinical Considerations

Disease-Associated Maternal and/or Embryo-Fetal Risk

Poorly controlled diabetes in pregnancy increases the maternal risk for diabetic ketoacidosis, preeclampsia, spontaneous abortions, preterm delivery, and delivery complications. Poorly controlled diabetes increases the fetal risk for major birth defects, stillbirth, and macrosomia related morbidity.

Data

Human Data

Published data from 5 randomized controlled trials of 441 pregnant women with diabetes mellitus treated with insulin aspart during the late 2ndtrimester of pregnancy did not identify an association of insulin aspart with major birth defects or adverse maternal or fetal outcomes. However, these studies cannot definitely establish the absence of any risk because of methodological limitations, including a variable duration of treatment and small size of the

majority of the trials.

Animal Data

Fertility, embryo-fetal and pre- and postnatal development studies have been performed with insulin aspart and regular human insulin in rats and rabbits. In a combined fertility and embryo-fetal development study in rats, insulin aspart was administered before mating, during mating, and throughout pregnancy. Further, in a pre- and postnatal development study insulin aspart was given throughout pregnancy and during lactation to rats. In an embryo-fetal development study insulin aspart was given to female rabbits during organogenesis. The effects of insulin aspart did not differ from those observed with subcutaneous regular human insulin. Insulin aspart, like human insulin, caused pre- and post-implantation losses and visceral/skeletal abnormalities in rats at a dose of 200 units/kg/day (approximately 32 times the human subcutaneous dose of 1 unit/kg/day, based on human exposure equivalents) and in rabbits at a dose of 10 units/kg/day (approximately three times the human subcutaneous dose of 1 unit/kg/day, based on human exposure equivalents). No significant effects were observed in rats at a dose of 50 units/kg/day and in rabbits at a dose of 3 units/kg/day. These doses are approximately 8 times the human subcutaneous dose of 1 unit/kg/day for rats and equal to the human subcutaneous dose of 1 unit/kg/day for rabbits, based on human exposure equivalents. The effects are considered secondary to maternal hypoglycemia.

8.2 Lactation

Risk Summary

There are no data on the presence of Insulin Aspart in human milk, the effects on the breastfed infant, or the effect on milk production. One small published study reported that exogenous insulin, including insulin aspart, was present in human milk. However, there is insufficient information to determine the effects of insulin aspart on the breastfed infant. The developmental and health benefits of breastfeeding should be considered along with the mother’s clinical need for Insulin Aspart, and any potential adverse effects on the breastfed infant from Insulin Aspart, or from the underlying maternal condition.

8.4 Pediatric Use

The safety and effectiveness of Insulin Aspart to improve glycemic control have been established in pediatric patients with diabetes mellitus. Use of Insulin Aspart for this indication is supported by evidence from an adequate and well-controlled study in 283 pediatric patients with type 1 diabetes mellitus aged 6 to 18 years and from studies in adults with diabetes mellitus [see Adverse Reactions (6.1), Clinical Pharmacology (12.3), and Clinical Studies (14)] .

8.5 Geriatric Use

Of the total number of patients (n=1,375) treated with Insulin Aspart in 3 controlled clinical studies, 2.6% (n=36) were 65 years of age or over. One-half of these patients had type 1 diabetes (18/1285) and the other half had type 2 diabetes (18/90). The HbA1cresponse to Insulin Aspart, as compared to regular human insulin, did not differ by age.

8.6 Renal Impairment

Patients with renal impairment may be at increased risk of hypoglycemia and may require more frequent Insulin Aspart dose adjustment and more frequent blood glucose monitoring [see Warnings and Precautions (5.3) and Clinical Pharmacology (12.3)].

8.7 Hepatic Impairment

Patients with hepatic impairment may be at increased risk of hypoglycemia and may require more frequent Insulin Aspart dose adjustment and more frequent blood glucose monitoring [see Warnings and Precautions (5.3) and Clinical Pharmacology (12.3)].

10 OVERDOSAGE

Excess insulin administration may cause hypoglycemia and hypokalemia [see Warnings and Precautions (5.3, 5.6)] . Mild episodes of hypoglycemia usually can be treated with oral glucose. Adjustments in drug dosage, meal patterns, or exercise may be needed. More severe episodes with coma, seizure, or neurologic impairment may be treated with intramuscular/subcutaneous glucagon or concentrated intravenous glucose. Sustained carbohydrate intake and observation may be necessary because hypoglycemia may recur after apparent clinical recovery. Hypokalemia must be corrected appropriately.

11 DESCRIPTION

Insulin aspart is a rapid-acting human insulin analog homologous with regular human insulin with the exception of a single substitution of the amino acid proline by aspartic acid in position B28, and is produced by recombinant DNA technology utilizing Saccharomyces cerevisiae(baker's yeast). Insulin aspart has the empirical formula C256H381N65079S6and a molecular weight of 5825.8 Da.

Insulin Aspart injection is a sterile, clear, and colorless solution for subcutaneous or intravenous use. Each mL contains 100 units of insulin aspart and the inactive ingredients: disodium hydrogen phosphate dihydrate (1.25 mg), glycerin (16.0 mg), metacresol (1.72 mg), phenol (1.50 mg), sodium chloride (0.58 mg), zinc (19.6 mcg), and Water for Injection, USP. Insulin Aspart has a pH of 7.2-7.6. Hydrochloric acid 10% and/or sodium hydroxide 10% may be added to adjust pH.

13 NONCLINICAL TOXICOLOGY

13.1 Carcinogenesis, Mutagenesis, Impairment of Fertility

Standard 2-year carcinogenicity studies in animals have not been performed to evaluate the carcinogenic potential of Insulin Aspart. In 52-week studies, Sprague-Dawley rats were dosed subcutaneously with Insulin Aspart at 10, 50, and 200 units/kg/day (approximately 2, 8, and 32 times the human subcutaneous dose of 1.0 units/kg/day, based on units/body surface area, respectively). At a dose of 200 units/kg/day, Insulin Aspart increased the incidence of mammary gland tumors in females when compared to untreated controls. The relevance of these findings to humans is unknown.

Insulin Aspart was not genotoxic in the following tests: Ames test, mouse lymphoma cell forward gene mutation test, human peripheral blood lymphocyte chromosome aberration test, in vivomicronucleus test in mice, and in ex vivoUDS test in rat liver hepatocytes.

In fertility studies in male and female rats, at subcutaneous doses up to 200 units/kg/day (approximately 32 times the human subcutaneous dose, based on units/body surface area), no direct adverse effects on male and female fertility, or general reproductive performance of animals was observed.

13.2 Animal Toxicology and/or Pharmacology

In standard biological assays in mice and rabbits, one unit of Insulin Aspart has the same glucose-lowering effect as one unit of regular human insulin.

14 CLINICAL STUDIES

14.1 Overview of Clinical Studies

The safety and effectiveness of subcutaneous Insulin Aspart were compared to regular human insulin in 596 type 1 diabetes adult, 187 pediatric type 1 diabetes, and 91 adult type 2 diabetes patients using NPH as basal insulin (see Tables 3, 4, 5). The reduction in glycated hemoglobin (HbA1c) was similar to regular human insulin.

The safety and effectiveness of Insulin Aspart administered by continuous subcutaneous insulin infusion (CSII) by external pump were compared to buffered regular human insulin (administered by CSII), to lispro (administered by CSII) and compared to Insulin Aspart injections and NPH injection. Overall, the reduction in HbA1cwas similar to the comparator.

14.2 Clinical Studies in Adult and Pediatric Patients with Type 1 Diabetes with Subcutaneous Injections

Type 1 Diabetes – Adults (see Table 3)

Two 24-week, open‑label, active-controlled studies were conducted to compare the safety and efficacy of Insulin Aspart to regular human insulin injection in adult patients with type 1 diabetes. Because the two study designs and results were similar, data are shown for only one study (see Table 3).

The mean age of the trial population was 39 years and mean duration of diabetes was 15.7 years. Fifty-one percent were male. Ninety-four percent were Caucasian, 2% were Black and 4% were Other. The mean BMI was approximately 25.6 kg/m^2.

Insulin Aspart was administered by subcutaneous injection immediately prior to meals and regular human insulin was administered by subcutaneous injection 30 minutes before meals. NPH insulin was administered as the basal insulin in either single or divided daily doses. Changes in HbA1cwere comparable for the two treatment regimens in this study (Table 3).

Table 3. Type 1 Diabetes Mellitus – Adult (Insulin Aspart plus NPH insulin vs. regular human insulin plus NPH insulin)

 | Insulin Aspart + NPH; (n=596) | Regular Human Insulin+ NPH; (n=286)
Baseline HbA1c(%)* | 7.9 ±1.1 | 8.0 ± 1.2
Change from Baseline HbA1c(%) | -0.1 ± 0.8 | 0.0 ± 0.8
Treatment Difference in HbA1c, Mean (95% confidence interval) | -0.2 (-0.3, -0.1)

*Values are Mean ± SD

Type 1 Diabetes – Pediatric (seeTable 4)

The efficacy of Insulin Aspart to improve glycemic control in pediatric patients with type 1 diabetes mellitus is based on an adequate and well-controlled trial of regular human insulin in pediatric patients with type 1 diabetes mellitus (Table 4). This 24-week, parallel-group study of pediatric patients with type 1 diabetes (n=283), aged 6 to 18 years, compared two subcutaneous multiple-dose treatment regimens: Insulin Aspart (n=187) or regular human insulin (n=96). NPH insulin was administered as the basal insulin. Similar effects on HbA1cwere observed in both treatment groups (Table 4).

Subcutaneous administration of Insulin Aspart and regular human insulin have also been compared in pediatric patients with type 1 diabetes (n=26) aged 2 to 6 years with similar effects on HbA1c.

Table 4. Pediatric Subcutaneous Administration of Insulin Aspart in Type 1 Diabetes(24 weeks; n=283)

 | Insulin Aspart + NPH; (n=187) | Regular Human Insulin+ NPH; (n=96)
Baseline HbA1c(%)* | 8.3 ± 1.2 | 8.3 ± 1.3
Change from Baseline HbA1c(%) | 0.1± 1.0 | 0.1± 1.1
Treatment Difference in HbA1c,Mean (95% confidence interval) | -0.2 (-0.5, 0.1)

*Values are Mean ± SD

14.3 Clinical Studies in Adults with Type 2 Diabetes with Subcutaneous Injections

Type 2 Diabetes - Adults (seeTable 5)

One six-month, open-label, active-controlled study was conducted to compare the safety and efficacy of Insulin Aspart to regular human insulin in patients with type 2 diabetes (Table 5).

The mean age of the trial population was 56.6 years and mean duration of diabetes was 12.7 years. Sixty-three percent were male. Seventy-six percent were Caucasian, 9% were Black and 15% were Other. The mean BMI was approximately 29.7 kg/m^2.

Insulin Aspart was administered by subcutaneous injection immediately prior to meals and regular human insulin was administered by subcutaneous injection 30 minutes before meals. NPH insulin was administered as the basal insulin in either single or divided daily doses. Changes in HbA1cwere comparable for the two treatment regimens.

Table 5. Subcutaneous Insulin Aspart Administration in Type 2 Diabetes(6 months; n=176)

 | Insulin Aspart + NPH; (n=90) | Regular Human Insulin + NPH; (n=86)
Baseline HbA1c(%)* | 8.1 ± 1.2 | 7.8 ± 1.1
Change from Baseline HbA1c(%) | -0.3 ± 1.0 | -0.1 ± 0.8
Treatment Difference in HbA1c,Mean (95% confidence interval) | - 0.1 (-0.4, 0.1)

*Values are Mean ± SD

14.4 Clinical Studies in Adults and Pediatrics with Type 1 Diabetes Using Continuous Subcutaneous Insulin Infusion (CSII) by External Pump

Type 1 Diabetes – Adult (seeTable 6)

Two open-label, parallel design studies (6 weeks [n=29] and 16 weeks [n=118]) compared Insulin Aspart to buffered regular human insulin (Velosulin) in adults with type 1 diabetes receiving a subcutaneous infusion with an external insulin pump.

The mean age of the trial population was 42.3 years. Thirty-nine percent were male. Ninety-eight percent were Caucasian and 2% were Black.

The two treatment regimens had comparable changes in HbA1c.

Table 6. Adult Insulin Pump Study in Type 1 Diabetes(16 weeks; n=118)

 | Insulin Aspart; (n=59) | Buffered human insulin; (n=59)
Baseline HbA1c(%)* | 7.3 ± 0.7 | 7.5 ± 0.8
Change from Baseline HbA1c(%) | 0.0 ± 0.5 | 0.2 ± 0.6
Treatment Difference in HbA1c,Mean (95% confidence interval) | 0.2 (-0.1, 0.4)

*Values are Mean ± SD

Type 1 Diabetes – Pediatric (seeTable 7)

A randomized, 16-week, open-label, parallel design study of pediatric patients with type 1 diabetes (n=298) aged 4-18 years compared two subcutaneous infusion regimens administered via an external insulin pump: Insulin Aspart (n=198) or insulin lispro (n=100). These two treatments resulted in comparable changes from baseline in HbA1c(see Table 7).

Table 7. Pediatric Insulin Pump Study in Type 1 Diabetes(16 weeks; n=298)

 | Insulin Aspart; (n=198) | Lispro; (n=100)
Baseline HbA1c(%)* | 8.0 ± 0.9 | 8.2 ± 0.8
Change from Baseline HbA1c(%) | -0.1 ± 0.8 | -0.1 ± 0.7
Treatment Difference in HbA1c,Mean (95% confidence interval) | -0.1 (-0.3, 0.1)

*Values are Mean ± SD

14.5 Clinical Studies in Adults with Type 2 Diabetes Using Continuous Subcutaneous Insulin Infusion (CSII) by External Pump

Type 2 Diabetes – Adults (seeTable 8)

An open-label, 16-week parallel design trial compared pre-prandial Insulin Aspart injection in conjunction with NPH injections to Insulin Aspart administered by continuous subcutaneous infusion in 127 adults with type 2 diabetes.

The mean age of the trial population was 55.1 years. Sixty-four percent were male. Eighty percent were Caucasian, 12% were Black and 8% were Other. The mean BMI was approximately 32.2 kg/m^2.

The two treatment groups had similar reductions in HbA1c(Table 8).

Table 8. Pump Therapy in Type 2 Diabetes(16 weeks; n=127)

 | Insulin Aspart pump; (n=66) | Insulin Aspart + NPH; (n=61)
Baseline HbA1c(%)* | 8.2 ± 1.4 | 8.0 ± 1.1
Change from Baseline HbA1c(%) | -0.6 ± 1.1 | -0.5 ± 0.9
Treatment Difference in HbA1c,Mean (95% confidence interval) | 0.1 (-0.3, 0.4)

*Values are Mean ± SD

16 HOW SUPPLIED/STORAGE AND HANDLING

Insulin Aspart injection 100 units/mL (U-100) is available as a clear and colorless solution in:

Five 3 mL single-patient-use PenFill prefilled cartridges* per carton

*Insulin Aspart PenFill cartridges are designed for use with compatible insulin delivery devices with NovoFine disposable needles. FlexPen can be used with NovoFine or NovoTwist disposable needles.

The Insulin Aspart FlexPen dials in 1-unit increments.

NDC: 70518-3865-00

PACKAGING: 5 in 1 CARTON, 3 mL in 1 SYRINGE PLASTIC , TYPE 2

Dispense in the original sealed carton with the enclosed Instructions for Use. Store unused Insulin Aspart in a refrigerator between 2°C to 8°C (36°F to 46°F). Do not freeze Insulin Aspart and do not use Insulin Aspart if it has been frozen. Do not expose Insulin Aspart to excessive heat or light. Do not withdraw Insulin Aspart into a syringe and store for later use.

Always remove and discard the needle after each injection from the Insulin Aspart FlexPen and store without a needle attached.

*For insulin pump use, the total in-use time is 19 days, including 7 days pump in-use time.

Storage in External Insulin Pump:

Change the Insulin Aspart in the pump reservoir at least every 7 days or in accordance to the pump user manual, whichever is shorter, or after exposure to temperatures that exceed 37°C (98.6°F).

Storage of Diluted Insulin Aspart

This Insulin Aspart product diluted with Insulin Diluting Medium for NovoLog (insulin aspart) to a concentration equivalent to U-10 or equivalent to U-50 prepared as indicated under Dosage and Administration (2.2) may remain in patient use at temperatures up to 30°C (86°F) for 28 days.

Storage of Insulin Aspart in Intravenous Infusion Fluids

Infusion bags prepared as indicated under Dosage and Administration (2.2) are stable at room temperature for 24 hours. Some insulin will be initially adsorbed to the material of the infusion.

Repackaged and Distributed By:

Remedy Repack, Inc.

625 Kolter Dr. Suite #4 Indiana, PA 1-724-465-8762

17 PATIENT COUNSELING INFORMATION

Advise the patient to read the FDA-approved patient labeling (Patient Information and Instructions for Use).

Never Share an Insulin Aspart FlexPen, PenFill Cartridge or PenFill Cartridge Device between Patients

Advise patients that they must never share Insulin Aspart FlexPen, PenFill cartridge or PenFill cartridge devices with another person even if the needle is changed, because doing so carries a risk for transmission of blood-borne pathogens. Advise patients using Insulin Aspart vials not to share needles or syringes with another person. Sharing poses a risk for transmission of blood-borne pathogens [see Warnings and Precautions (5.1)] .

Hyperglycemia or Hypoglycemia

Inform patients that hypoglycemia is the most common adverse reaction with insulin. Instruct patients on self-management procedures including glucose monitoring, proper injection technique, and management of hypoglycemia and hyperglycemia, especially at initiation of Insulin Aspart therapy. Instruct patients on handling of special situations such as intercurrent conditions (illness, stress, or emotional disturbances), an inadequate or skipped insulin dose, inadvertent administration of an increased insulin dose, inadequate food intake, and skipped meals. Instruct patients on the management of hypoglycemia [see Warnings and Precautions (5.3)] .

Inform patients that their ability to concentrate and react may be impaired as a result of hypoglycemia. Advise patients who have frequent hypoglycemia or reduced or absent warning signs of hypoglycemia to use caution when driving or operating machinery.

Advise patients that changes in insulin regimen can predispose to hyperglycemia or hypoglycemia and that changes in insulin regimen should be made under close medical supervision [see Warnings and Precautions (5.2)] .

Hypoglycemia with Medication Errors

Instruct patients to always check the insulin label before each injection to avoid mix-ups between insulin products [see Warnings and Precautions (5.3)] .

Hypersensitivity Reactions

Advise patients that hypersensitivity reactions have occurred with Insulin Aspart. Inform patients of the symptoms of hypersensitivity reactions [see Warnings and Precautions (5.4)] .

Patients Using Continuous Subcutaneous Insulin Pumps

- Train patients in both intensive insulin therapy with multiple injections and in the function of their pump and pump accessories.
- This Insulin Aspart product can be used with continuous subcutaneous insulin infusion pumps labeled for use with NOVOLOG (insulin aspart) - refer to the insulin pump user manual to see if NOVOLOG can be used. See recommended infusion sets in the insulin pump user manual.
- Instruct patients to replace insulin in the reservoir at least every 7 days or according to the user manual, whichever is shorter, infusion sets and infusion set insertion sites should be changed in according to the manufacturer’s user manual. By following this schedule, patients avoid insulin degredation, infusion set occlusion, and loss of the insulin preservative.
- Instruct patients to discard insulin exposed to temperatures higher than 37°C (98.6°F).
- Instruct patients to inform physician and select a new site for infusion if infusion site becomes erythematous, pruritic, or thickened.
- Instruct patients of the risk of rapid hyperglycemia and ketosis due to pump malfunction, infusion set occlusion, leakage, disconnection or kinking, and degraded insulin. If these problems cannot be promptly corrected, instruct patients to resume therapy with subcutaneous insulin injection and contact their physician [see Warnings and Precautions (5) and How Supplied/Storage and Handling (16.2)] .
- Instruct patients of the risk of hypoglycemia from pump malfunction. If these problems cannot be promptly corrected, instruct patients to resume therapy with subcutaneous insulin injection and contact their physician [see Warnings and Precautions (5) and How Supplied/Storage and Handling (16.2)] .

Distributed By: RemedyRepack Inc.

625 Kolter Drive, Indiana, PA 15701

(724) 465-8762

PATIENT INFORMATION.

Insulin Aspart[ in∙suh∙luhn a∙sprt]

injection, for subcutaneous or intravenous use

This product is NovoLog (insulin aspart).

Do not share your Insulin Aspart FlexPen, PenFill cartridge or PenFill cartridge compatible insulin delivery device with other people, even if the needle has been changed. You may give other people a serious infection, or get a serious infection from them.

What is Insulin Aspart?

- Insulin Aspart is a man-made insulin that is used to control high blood sugar in adults and children with diabetes mellitus.

Who should not take Insulin Aspart?

Do not take Insulin Aspart if you:

- are having an episode of low blood sugar (hypoglycemia).
- have an allergy to Insulin Aspart or any of the ingredients in Insulin Aspart.

Before taking Insulin Aspart, tell your healthcare provider about all your medical conditions including, if you are:

- pregnant, planning to become pregnant, or are breastfeeding.
- taking new prescription or over-the-counter medicines, vitamins, or herbal supplements.

Before you start taking Insulin Aspart, talk to your healthcare provider about low blood sugar and how to manage it.

How should I take Insulin Aspart?

- Read the Instructions for Usethat come with your Insulin Aspart.
- Take Insulin Aspart exactly as your healthcare provider tells you to.
- Insulin Aspart starts acting fast.You should eat a meal within 5 to 10 minutes after you take your dose of Insulin Aspart.
- Know the type and strength of insulin you take. Do notchange the type of insulin you take unless your healthcare provider tells you to. The amount of insulin and the best time for you to take your insulin may need to change if you take different types of insulin.
- Check your blood sugar levels.Ask your healthcare provider what your blood sugars should be and when you should check your blood sugar levels.
- Do not reuse or share your needles with other people.You may give other people a serious infection or get a serious infection from them.
- Insulin Aspart can be injected under the skin (subcutaneously) of your stomach area (abdomen), buttocks, upper legs (thighs) or upper arms, or by continuous infusion under the skin (subcutaneously) through an insulin pump into an area of your body recommended in the instructions that come with your insulin pump.
- Change (rotate) your injection sites within the area you choose with each doseto reduce your risk of getting lipodystrophy (pits in skin or thickened skin) and localized cutaneous amyloidosis (skin with lumps) at the injection sites.
- Do notuse the exact same spot for each injection.
- Do notinject where the skin has pits, is thickened, or has lumps.
- Do notinject where the skin is tender, bruised, scaly or hard, or into scars or damaged skin.

What should I avoid while taking Insulin Aspart?

While taking Insulin Aspart do not:

- Drive or operate heavy machinery, until you know how Insulin Aspart affects you.
- Drink alcohol or use prescription or over-the-counter medicines that contain alcohol.

What are the possible side effects of Insulin Aspart?

Insulin Aspart may cause serious side effects that can lead to death, including:

Low blood sugar (hypoglycemia).Signs and symptoms that may indicate low blood sugar include:

- dizziness or light-headedness
- blurred vision
- anxiety, irritability, or mood changes
- sweating
- slurred speech
- hunger
- confusion
- shakiness
- headache
- fast heart beat

Your insulin dose may need to change because of:

- change in level of physical activity or exercise
- increased stress
- change in diet
- weight gain or loss
- illness

Other common side effects of Insulin Aspart may include:

- low potassium in your blood (hypokalemia), reactions at the injection site, itching, rash, serious allergic reactions (whole body reactions), skin thickening or pits at the injection site (lipodystrophy), weight gain, and swelling of your hands and feet.

Get emergency medical help if you have:

- trouble breathing, shortness of breath, fast heartbeat, swelling of your face, tongue, or throat, sweating, extreme drowsiness, dizziness, confusion.

These are not all the possible side effects of Insulin Aspart. Call your doctor for medical advice about side effects. You may report side effects to FDA at 1-800-FDA-1088.

General information about the safe and effective use of Insulin Aspart.

Medicines are sometimes prescribed for purposes other than those listed in a Patient Information leaflet. You can ask your pharmacist or healthcare provider for information about Insulin Aspart that is written for health professionals. Do not use Insulin Aspart for a condition for which it was not prescribed. Do not give Insulin Aspart to other people, even if they have the same symptoms that you have. It may harm them.

What are the ingredients in Insulin Aspart?

Active Ingredient:insulin aspart

Inactive Ingredients:disodium hydrogen phosphate dihydrate, glycerin, metacresol, phenol, sodium chloride, zinc, and Water for Injection, USP. Hydrochloric acid 10% and/or sodium hydroxide 10% may be added to adjust pH.

Manufactured by:Novo Nordisk Inc., Plainsboro, NJ 08536, U.S. License Number 1261

For more information, call 1-800-727-6500.

This Patient Information has been approved by the U.S. Food and Drug Administration.

Revised: 02/2023

INSTRUCTIONS FOR USE

Insulin Aspart [in∙suh∙luhn a∙sprt]

injection, for subcutaneous or intravenous use

10 mL multiple-dose vial (100 units/mL, U-100)

This product is NovoLog (insulin aspart).

Read this Instructions for Use before you start taking Insulin Aspart and each time you get a refill. There may be new information. This information does not take the place of talking to your healthcare provider about your medical condition or your treatment.

Supplies you will need to give your Insulin Aspart injection:

- 10 mL Insulin Aspart vial
- insulin syringe and needle
- alcohol swabs

Preparing your Insulin Aspart dose:

- Wash your hands with soap and water.
- Before you start to prepare your injection, check the Insulin Aspart label to make sure that you are taking the right type of insulin. This is especially important if you use more than 1 type of insulin.
- Insulin Aspart should look clear and colorless. Do notuse Insulin Aspart if it is thick, cloudy, or is colored.
- Do notuse Insulin Aspart past the expiration date printed on the label.

Step 1:Pull off the tamper resistant cap (See Figure A).

Step 2:Wipe the rubber stopper with an alcohol swab (See Figure B).

Step 3:Hold the syringe with the needle pointing up. Pull down on the plunger until the black tip reaches the line for the number of units for your prescribed dose (See Figure C).

Step 4:Push the needle through the rubber stopper of the Insulin Aspart vial (See Figure D).

Step 5:Push the plunger all the way in. This puts air into the Insulin Aspart vial (See Figure E).

Step 6:Turn the Insulin Aspart vial and syringe upside down and slowly pull the plunger down until the black tip is a few units past the line for your dose (See Figure F).

- If there are air bubbles, tap the syringe gently a few times to let any air bubbles rise to the top (See Figure G).

Step 7:Slowly push the plunger up until the black tip reaches the line for your Insulin Aspart dose (See Figure H).

Step 8:Check the syringe to make sure you have the right dose of Insulin Aspart.

Step 9:Pull the syringe out of the vial’s rubber stopper (See Figure I).

- Giving your Injection:

- Inject your Insulin Aspart exactly as your healthcare provider has shown you. Your healthcare provider should tell you if you need to pinch the skin before injecting.
- Insulin Aspart can be injected under the skin (subcutaneously) of your stomach area, buttocks, upper legs or upper arms, infused in an insulin pump (continuous subcutaneous infusion into an area of your body recommended in the instructions that come with your insulin pump), or given through a needle in your arm (intravenously) by your healthcare provider.
- If you inject Insulin Aspart, change (rotate) your injection sites within the area you choose for each dose to reduce your risk of getting lipodystrophy (pits in skin or thickened skin) and localized cutaneous amyloidosis (skin with lumps) at the injection sites. Do notuse the same injection site for each injection. Do notinject where the skin has pits, is thickened, or has lumps. Do notinject where the skin is tender, bruised, scaly or hard, or into scars or damaged skin.
- If you use Insulin Aspart in an insulin pump, you should change your infusion set and insertion site according to the manufacturer’s user manual. This Insulin Aspart product can be used with the continuous subcutaneous insulin infusion pumps labeled for use with NovoLog (insulin aspart) - refer to the insulin pump user manual to see if NovoLog can be used. Insulin Aspart should be given into an area of your body recommended in the instructions that come with your insulin pump. Change (rotate) your insertion sites within the area you choose for each insertion to reduce your risk of getting lipodystrophy (pits in skin or thickened skin) and localized cutaneous amyloidosis (skin with lumps) at the insertion sites. Do not insert into the exact same spot for each insertion. Do not insert where the skin has pits, is thickened, or has lumps. Do not insert where the skin is tender, bruised, scaly or hard, or into scars or damaged skin. The insulin in the reservoir should be changed at least every 7 days or according to the pump user manual, whichever is shorter, even if you have not used all of the insulin.
- If you use Insulin Aspart in an insulin pump, see your insulin pump manual for instructions or talk to your healthcare provider.
- NPH insulin is the only type of insulin that can be mixed with Insulin Aspart. Do notmix Insulin Aspart with any other type of insulin.
- Insulin Aspart should onlybe mixed with NPH insulin if it is going to be injected right away under your skin (subcutaneously).
- Insulin Aspart should be drawn up into the syringe beforeyou draw up your NPH insulin.
- Talk to your healthcare provider if you are not sure about the right way to mix Insulin Aspart and NPH insulin.

Step 10: Choose your injection site (stomach area, buttocks, upper legs or upper arms) and wipe the skin with an alcohol swab. Let the injection site dry before you inject your dose (See Figure J).

(Figure J)

Step 11:Insert the needle into your skin. Push down on the plunger to inject your dose (See Figure K). The needle should remain in the skin for at least 6 seconds to make sure you have injected all the insulin.

Step 12:Pull the needle out of your skin. After that, you may see a drop of Insulin Aspart at the needle tip. This is normal and does not affect the dose you just received (See Figure L).

- If you see blood after you take the needle out of your skin, press the injection site lightly with a
- piece of gauze or an alcohol swab. Do notrub the area.

After your injection:

- Do notrecap the needle. Recapping the needle can lead to a needle stick injury.
- Put the empty insulin vials, used needles and syringes in a FDA-cleared sharps disposal container right away after use. Do not throw away (dispose of) loose needles and syringes and needles in your household trash.
- If you do not have a FDA-cleared sharps disposal container, you may use a household container that is:
- made of a heavy-duty plastic,
- can be closed with a tight-fitting, puncture-resistant lid, without sharps being able to come out,
- upright and stable during use,
- leak-resistant, and properly labeled to warn of hazardous waste inside the container.
- When your sharps disposal container is almost full, you will need to follow your community guidelines for the right way to dispose of your sharps disposal container. There may be state or local laws about how you should throw away used needles and syringes. For more information about the safe sharps disposal, and for specific information about sharps disposal in the state that you live in, go to the FDA’s website at: http://www.fda.gov/safesharpsdisposal.
  Do not dispose of your used sharps disposal container in your household trash unless your community guidelines permit this. Do not recycle your used sharps disposal container.

How should I store Insulin Aspart?

- Do notfreeze Insulin Aspart. Do notuse Insulin Aspart if it has been frozen.
- Keep Insulin Aspart away from heat or light.
- All unopened vials:
- Store unopened Insulin Aspart vials in the refrigerator at 36°F to 46°F (2°C to 8°C).
- Unopened vials may be used until the expiration date printed on the label, if they have been stored in the refrigerator.
- Unopened vials should be thrown away after 28 days, if they are stored at room temperature.
- After vials have been opened:
- Opened Insulin Aspart vials can be stored in the refrigerator at 36°F to 46°F (2°C to 8°C) or at room temperature below 86°F (30°C).
- Throw away all opened Insulin Aspart vials after 28 days, even if they still have insulin left in them.
- If using Insulin Aspart in a pump, throw away all opened Insulin Aspart vials after 19 days.

General information about the safe and effective use of Insulin Aspart

- Always use a new syringe and needle for each injection.
- Do not share syringes or needles.
- Keep Insulin Aspart vials, syringes, and needles out of the reach of children.

This Instructions for Use has been approved by the U.S. Food and Drug Administration.

INSTRUCTIONS FOR USE

Insulin Aspart [in∙suh∙luhn a∙sprt]

injection, for subcutaneous or intravenous use

PenFill®3 mL cartridge 100 units/mL (U-100)

This product is NovoLog (insulin aspart).

- Do not share your PenFill cartridge or PenFill cartridge compatible insulin delivery device with other people, even if the needle has been changed. You may give other people a serious infection, or get a serious infection from them.
- Your healthcare provider should show you or your caregiver how to inject Insulin Aspart the right way before you inject it for the first time.
- Insulin Aspart PenFill cartridge 100 units/mL is a prefilled, single-patient-use cartridgecontaining 300 units of Insulin Aspart.
- After you insert the PenFill cartridge in your device, you can use it for multiple injections. Read the instruction manualthat comes with your insulin delivery device for complete instructions on how to use the PenFill cartridge with the device.
- People who are blind or have vision problems should not use this PenFill cartridge without help from a person trained to use the PenFill cartridge with the device.
- If using a newInsulin Aspart PenFill cartridge, start with Step 1.
- If the Insulin Aspart PenFill cartridge has already been used, start with Step 2.

Supplies you will need to give your Insulin Aspart injection:

- Insulin Aspart PenFill cartridge
- Novo Nordisk 3 mL PenFill cartridge compatible insulin delivery device
- 1 new NovoFine, NovoFine Plus, or NovoTwist needle
- Alcohol swabs
- Adhesive bandage
- Cotton gauze
- A sharps container for throwing away used PenFill cartridges and needles. See “After your injection” at the end of these instructions.

(Figure A)

How to use the Insulin Aspart PenFill cartridge

- Wash your hands with soap and water.
- Before you start to prepare your injection, check theInsulin Aspart PenFill cartridge labelto make sure that it contains the insulin you need. This is especially important if you take more than 1 type of insulin.
- The tamper-resistant foil should be in place before the first use. If the foil has been broken or removed before your first use of the cartridge, do notuse it. Call Novo Nordisk at 1-800-727-6500.
- Carefully look at the cartridge and the insulin inside it. Check that the Insulin Aspart cartridge:
  - is not damaged, for example cracked or leaking
  - is not loose on the threaded end
- Insulin Aspart should look clear and colorless. Do notuse Insulin Aspart if it is cloudy or colored or if the threaded end is loose (See Figure B).

(Figure B)

Step 1:

- Insert a 3 mL cartridge with the threaded end first into your Novo Nordisk 3 mL PenFill cartridge compatible insulin delivery device (See Figure C).
- If you drop your device, check the insulin cartridge for damage such as cracks or leaking. If your cartridge is damaged, throw it away and use a new one.

(Figure C)

Prepare your device with a new needle

Step 2:

- Take a new needle,and tear off the paper tab. Always use a new needle for each injection to make sure the needle is free of germs (sterile) and to prevent blocked needles. Do not attach a new needleto your device until you are ready to give your injection. Do not reuse or share your needles with other people. You may give others a serious infection, or get a serious infection from them.
- Be careful not to bend or damage the needle before you use it.
- Push the needle straight onto the device. Turn the needle clockwise until it is on tight (See Figure D).

(Figure D)

Step 3:

- Pull off the outer needle cap(See Figure E) . Do notthrow it away. You will need it after the injection to safely remove the needle.

(Figure E)

Step 4:

- Pull off the inner needle capand throw it away (See Figure F). Do nottry to put the inner needle cap back on the needle.

(Figure F)

A drop of insulin may appear at the needle tip. This is normal, but you must still check the insulin flow.

1. Check the insulin flow

Step 5:

- Small amounts of air may collect in the cartridge during normal use. You must do an airshot before each injection to avoid injecting air and to make sure you receive the prescribed dose of your medicine.
- Do the airshot as described in the instruction manual that comes with your device.
- Keep testing your Novo Nordisk 3 mL PenFill cartridge compatible insulin delivery device until you see insulin at the needle tip. If you still do not see a drop of insulin after 6 times, change the needle and repeat this step. This makes sure that any air bubbles are removed and that insulin is getting through the needle (See Figure G).

(Figure G)

Select your dose

Step 6:

- Check to make sure that the dose counter is set to 0.
- Turn the dose selector clockwise to select the dose you needto inject (See Figure H). The pointer should line up with your dose. When turning the dose selector, be careful not to press the dose button as insulin will come out. You will hear a click for every single unit dialed. Do notset the dose by counting the number of clicks you hear because you may get an incorrect dose.
- Refer to your insulin delivery device manual if necessary.

(Figure H)

Inject your dose

Step 7:

- Do the injection exactly as shown to you by your healthcare provider. Your healthcare provider should tell you if you need to pinch the skin before injecting.
- Insulin Aspart can be injected under the skin (subcutaneously) of your stomach area (abdomen), buttocks, upper legs (thighs), or upper arms (See Figure I).

- (Figure I)

- Change (rotate) your injection sites within the area you choose for each dose to reduce your risk of getting lipodystrophy (pits in skin or thickened skin) and localized cutaneous amyloidosis (skin with lumps) at the injection sites. Do not use the same injection site for each injection. Do not inject where the skin has pits, is thickened, or has lumps. Do not inject where the skin is tender, bruised, scaly or hard, or into scars or damaged skin.
- Clean your injection site with an alcohol swab. Let your skin dry. Do not touch this area again before injecting.
- Insert the needle into your skin. Press and hold down the dose button until the dose counter shows “0”. Continue to keep the dose button pressed and keep the needle in your skin and slowly count to 6 (see Figure J).
- Remove the needle from your skin.

(Figure J)

You may see a drop of Insulin Aspart at the needle tip after injecting. This is normal and has no effect on the dose you just received. If blood appears after you take the needle out of your skin, press the injection site lightly with a cotton gauze and cover with an adhesive bandage, if necessary. Do not rub the area.

After your injection

Step 8:

- Lay your outer needle cap on a flat surface. Carefully, lead the needle tip into the outer needle cap without touching the needle (See Figure K) and push the outer needle cap completely on.

(Figure K)

- Hold the black cartridge holder on the insulin delivery device and unscrew the needle counterclockwise (See Figure L).

(Figure L)

- Throw away (dispose of) the needle in an FDA-cleared sharps container as your healthcare professional has instructed you.
- Put your empty Insulin Aspart PenFill cartridge and used needles in a FDA-cleared sharps disposal container right away after use. Do not throw away (dispose of) loose needles and PenFill cartridges in your household trash.
- If you do not have a FDA-cleared sharps disposal container, you may use a household container that is:
  - made of a heavy-duty plastic,
  - can be closed with a tight-fitting, puncture-resistant lid, without sharps being able to come out,
  - upright and stable during use, and
  - leak-resistant and properly labeled to warn of hazardous waste inside the container.
- When your sharps disposal container is almost full, you will need to follow your community guidelines for the right way to dispose of your sharps disposal container. There may be state or local laws about how you should throw away used needles and syringes. Do not reuse or share your needles or syringes with other people. For more information about the safe sharps disposal, and for specific information about sharps disposal in the state that you live in, go to the FDA’s website at: http://www.fda.gov/safesharpsdisposal.
- Do not dispose of your used sharps disposal container in your household trash unless your community guidelines permit this. Do not recycle your used sharps disposal container.

Step 9:

- Keep the 3 mL PenFill cartridge in the device. Do notstore your device with a needle attached. This will prevent infection or leakage of insulin and will make sure that you receive the right dose of Insulin Aspart.
- Put the pen cap onyour device after each use to protect the insulin from light (See Figure M).

(Figure M)

How should I store my Insulin Aspart PenFill cartridge?

- Do notfreeze Insulin Aspart. Do notuse Insulin Aspart if it has been frozen.
- Keep Insulin Aspart away from heat or light.
- Store the Insulin Aspart PenFill cartridge without the needle attached.

Before use:

- Store unused Insulin Aspart PenFill cartridges in the refrigerator at 36°F to 46°F (2°C to 8°C).
- Unused PenFill cartridges may be used until the expiration date printed on the label, if kept in the refrigerator.
- If Insulin Aspart is stored mistakenly outside of refrigeration between 47°F (9°C) to 86°F (30°C) prior to first use, it should be used within 28 days or thrown away.

PenFill cartridges in use:

- Store the PenFill cartridge you are currently using in the insulin delivery device at room temperature below 86°F (30°C) for up to 28 days. Do not refrigerate.
- The Insulin Aspart PenFill cartridge you are using should be thrown away after 28 days, even if it still has insulin left in it.

General Information about the safe and effective use of Insulin Aspart.

- Keep Insulin Aspart PenFill cartridges and needles out of the reach of children.
- Do notshare Insulin Aspart PenFill cartridges or needles with other people. You may give other people a serious infection, or get a serious infection from them.
- Always carry extra insulin of the same type(s) you use in case of loss or damage.

This Instructions for Use has been approved by the U.S. Food and Drug Administration.

© 2023 Novo Nordisk

INSTRUCTIONS FOR USE

Insulin Aspart [in∙suh∙luhn a∙sprt]

injection, for subcutaneous or intravenous use

3 mL FlexPen®prefilled pen (100 units/mL, U-100)

This product is NovoLog (insulin aspart).

Introduction

Please read the following instructions carefully before using your Insulin Aspart FlexPen.

Do not share your Insulin Aspart FlexPen with other people, even if the needle has been changed. You may give other people a serious infection, or get a serious infection from them.

Insulin Aspart FlexPen is a disposable, single-patient-use, dial-a-dose insulin pen. You can select doses from 1 to 60 units in increments of 1 unit. Insulin Aspart FlexPen is designed to be used with NovoFine, NovoFine Plus or NovoTwist needles.

- Δ People who are blind or have vision problems should not use this Pen without help from a person trained to use the Pen.

Getting ready

Make sure you have the following items:

- Insulin Aspart FlexPen
- New NovoFine, NovoFine Plus or NovoTwist needle
- Alcohol swabs

Preparing your Insulin Aspart FlexPen

Wash your hands with soap and water. Before you start to prepare your injection, check the label to make sure that you are taking the right type of insulin. This is especially important if you take more than 1 type of insulin. Insulin Aspart should look clear and colorless. Do not use your Insulin Aspart FlexPen if the liquid contains particles or is colored.

A. Pull off the pen cap (see diagram A).

Wipe the rubber stopper with an alcohol swab.

B. Attaching the needle

Remove the protective tab from a disposable needle.

Screw the needle tightly onto your FlexPen. It is important that the needle is put on straight (see diagram B).

Never place a disposable needle on your Insulin Aspart FlexPen until you are ready to take your injection.

C.Pull off the big outer needle cap (see diagram C).

D.Pull off the inner needle cap and throw it away (dispose of it) (see diagram D).

- ΔAlways use a new needle for each injection to make sure the needle is free of germs (sterile) and to prevent blocked needles. Do not reuse or share your needles with other people. You may give other people a serious infection, or get a serious infection from them.
- ΔBe careful not to bend or damage the needle before use.
- ΔTo reduce the risk of unexpected needle sticks, never put the inner needle cap back on the needle.

Giving the airshot before each injection

Before each injection small amounts of air may collect in the cartridge during normal use. To avoid injecting air and to ensure proper dosing:

E.Turn the dose selector to select 2 units (see diagram E).

F.Hold your Insulin Aspart FlexPen with the needle pointing up. Tap the cartridge gently with your finger a few times to make any air bubbles collect at the top of the cartridge (see diagram F).

G.Keep the needle pointing upwards, press the push-button all the way in (see diagram G). The dose selector returns to 0.

A drop of insulin should appear at the needle tip. If not, change the needle and repeat the procedure no more than 6 times.

If you do not see a drop of insulin after 6 times, do not use the Insulin Aspart FlexPen and contact Novo Nordisk at 1-800-727-6500.

A small air bubble may remain at the needle tip, but it will not be injected.

Selecting your dose

Check and make sure that the dose selector is set at 0.

H.Turn the dose selector to the number of units you need to inject. The pointer should line up with your dose.

The dose can be corrected either up or down by turning the dose selector in either direction until the correct dose lines up with the pointer (see diagram H). When turning the dose selector, be careful not to press the push-button as insulin will come out.

You cannot select a dose larger than the number of units left in the cartridge.

You will hear a click for every single unit dialed. Do not set the dose by counting the number of clicks you hear because you may get an incorrect dose.

- Δ Do not use the cartridge scale printed on the cartridge to measure your dose of insulin.

Giving the injection

Do the injection exactly as shown to you by your healthcare provider. Your healthcare provider should tell you if you need to pinch the skin before injecting. Wipe the skin with an alcohol swab and let the area dry.

Insulin Aspart can be injected under the skin (subcutaneously) of your stomach area, buttocks, upper legs (thighs), or upper arms.

Change (rotate) your injection sites within the area you choose for each dose to reduce your risk of getting lipodystrophy (pits in skin or thickened skin) and localized cutaneous amyloidosis (skin with lumps) at the injection sites. Do notuse the same injection site for each injection. Do notinject where the skin has pits, is thickened, or has lumps. Do notinject where the skin is tender, bruised, scaly or hard, or into scars or damaged skin.

I.Insert the needle into your skin.

Inject the dose by pressing the push-button all the way in until the 0 lines up with the pointer (see diagram I). Be careful only to push the button when injecting.

Turning the dose selector will not inject insulin.

J.Keep the needle in the skin for at least 6 seconds, and keep the push-button pressed all the way in until the needle has been pulled out from the skin (see diagram J). This will make sure that the full dose has been given.

You may see a drop of insulin at the needle tip. This is normal and has no effect on the dose you just received. If blood appears after you take the needle out of your skin, press the injection site lightly with an alcohol swab. Do not rub the area.

After the injection

Do not recap the needle.Recapping can lead to a needle stick injury. Remove the needle from the Insulin Aspart FlexPen after each injection and dispose of it. This helps to prevent infection, leakage of insulin, and will help to make sure you inject the right dose of insulin.

If you do not have a sharps container, carefully slip the needle into the outer needle cap. Safely remove the needle and throw it away as soon as you can.

- The used Insulin Aspart FlexPen may be thrown away in your household trash after you have removed the needle.
- Put your used needles in a FDA-cleared sharps disposal container right away after use. Do not throw away (dispose of) loose needles in your household trash.
- If you do not have a FDA-cleared sharps disposal container, you may use a household container that is:
- made of a heavy-duty plastic,
- can be closed with a tight-fitting, puncture-resistant lid, without sharps being able to come out,
- upright and stable during use,
- leak-resistant, and
- properly labeled to warn of hazardous waste inside the container.
- When your sharps disposal container is almost full, you will need to follow your community guidelines for the right way to dispose of your sharps disposal container. There may be state or local laws about how you should throw away used needles and syringes. For more information about the safe sharps disposal, and for specific information about sharps disposal in the state that you live in, go to the FDA’s website at: http://www.fda.gov/safesharpsdisposal.
  Do not dispose of your used sharps disposal container in your household trash unless your community guidelines permit this. Do not recycle your used sharps disposal container.
- When there is not enough medicine left in your Insulin Aspart FlexPen for your prescribed dose, the Insulin Aspart FlexPen may be thrown away in your household trash after you have removed the needle. The Insulin Aspart FlexPen prevents the cartridge from being completely emptied. It is designed to deliver 300 units.

K. Put the pen cap on the Insulin Aspart FlexPen and store the Insulin Aspart FlexPen without the needle attached (see diagram K).

Storing without the needle attached helps prevent leaking, blocking of the needle, and air from entering the Pen.

How should I store Insulin Aspart FlexPen?

- Do notfreeze Insulin Aspart. Do notuse Insulin Aspart if it has been frozen.
- Keep Insulin Aspart away from heat or light.
- Store the Insulin Aspart FlexPen without the needle attached.
- Until first use:
- Store unused Insulin Aspart FlexPen in the refrigerator at 36°F to 46°F (2°C to 8°C).
- Unused FlexPen may be used until the expiration date printed on the label, if kept in the refrigerator.
- Unused Insulin Aspart FlexPen stored at room temperature should be thrown away after 28 days.
- In-use:
- Store the FlexPen you are currently using out of the refrigerator at room temperature below 86°F (30°C) for up to 28 days.
- The Insulin Aspart FlexPen you are using should be thrown away after 28 days, even if it still has insulin left in it.

Maintenance

For the safe and proper use of your FlexPen be sure to handle it with care. Avoid dropping your FlexPen as it may damage it. If you are concerned that your FlexPen is damaged, use a new one. You can clean the outside of your FlexPen by wiping it with a damp cloth. Do not soak or wash your FlexPen as it may damage it. Do not refill your FlexPen.

ΔRemove the needle from the Insulin Aspart FlexPen after each injection. This helps to ensure sterility, prevent leakage of insulin, and will help to make sure you inject the right dose of insulin for future injections.

ΔBe careful when handling used needles to avoid needle sticks and transfer of infectious diseases.

ΔKeep your Insulin Aspart FlexPen and needles out of the reach of children.

ΔUse Insulin Aspart FlexPen as directed to treat your diabetes.

Δ Do notshare your Insulin Aspart FlexPen or needles with other people. You may give other people a serious infection, or

get a serious infection from them.

ΔAlways use a new needle for each injection.

ΔNovo Nordisk is not responsible for harm due to using this insulin pen with products not recommended by Novo

Nordisk.

ΔAs a precautionary measure, always carry a spare insulin delivery device in case your Insulin Aspart FlexPen is lost or damaged.

ΔRemember to keep the disposable Insulin Aspart FlexPen with you. Do not leave it in a car or other location where it can get too hot or too cold.

This Instructions for Use has been approved by the U.S. Food and Drug Administration.

Repackaged and Distributed By:

Remedy Repack, Inc.

625 Kolter Dr. Suite #4 Indiana, PA 1-724-465-8762

PACKAGE LABEL

DRUG: Insulin Aspart

GENERIC: insulin aspart

DOSAGE: INJECTION, SOLUTION

ADMINSTRATION: INTRAVENOUS

NDC: 70518-3865-0

PACKAGING: 3 mL in 1 SYRINGE, PLASTIC

OUTER PACKAGING: 5 in 1 CARTON

ACTIVE INGREDIENT(S):

- INSULIN ASPART 100[iU] in 1mL

INACTIVE INGREDIENT(S):

- SODIUM PHOSPHATE, DIBASIC, DIHYDRATE
- GLYCERIN
- HYDROCHLORIC ACID
- METACRESOL
- PHENOL
- SODIUM CHLORIDE
- SODIUM HYDROXIDE
- ZINC